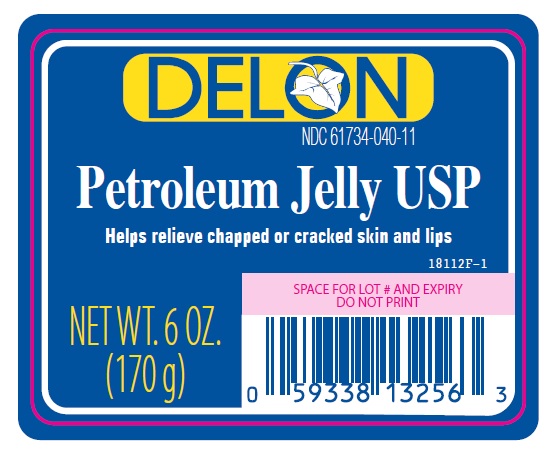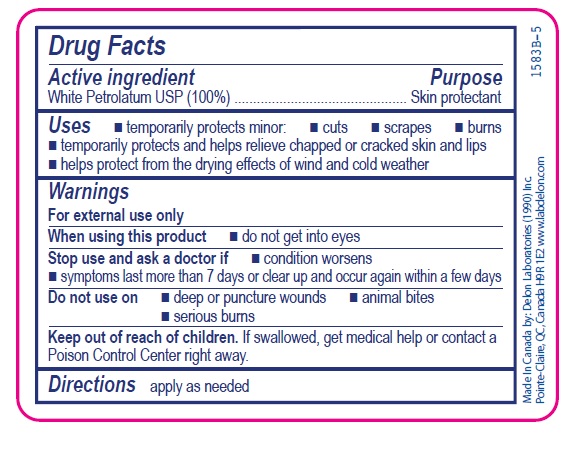 DRUG LABEL: Petroleum
NDC: 61734-040 | Form: JELLY
Manufacturer: Delon Laboratories (1990) Ltd
Category: otc | Type: HUMAN OTC DRUG LABEL
Date: 20241030

ACTIVE INGREDIENTS: PETROLATUM 100 g/100 g

Pet Jelly

Active ingredient

White Petrolatum USP (100%)

Purpose

Skin protectant

Uses

- temporarily protects minor:
- cuts
- scrapes
- burns
- temporarily protects and helps relieve chapped or cracked skin and lips
- helps protect from the drying effects of wind and cold weather

Warnings

For external use only

When using this product

- do not get into eyes

Stop use and ask a doctor if

- condition worsens
- symptoms last more than 7 days or clear up and occur again within a few days

Do not use on

- deep or puncture wounds
- animal bites
- serious burns

Keep out of reach of children. If swallowed, get medical help or contact a Poison Control Center right away.

Directions

apply as needed